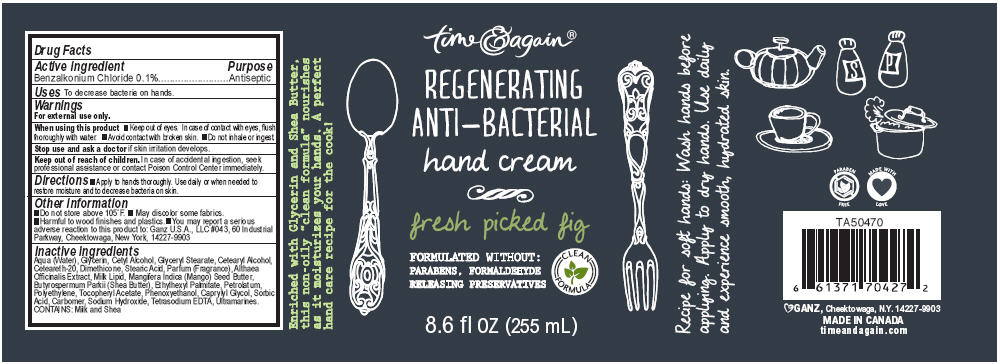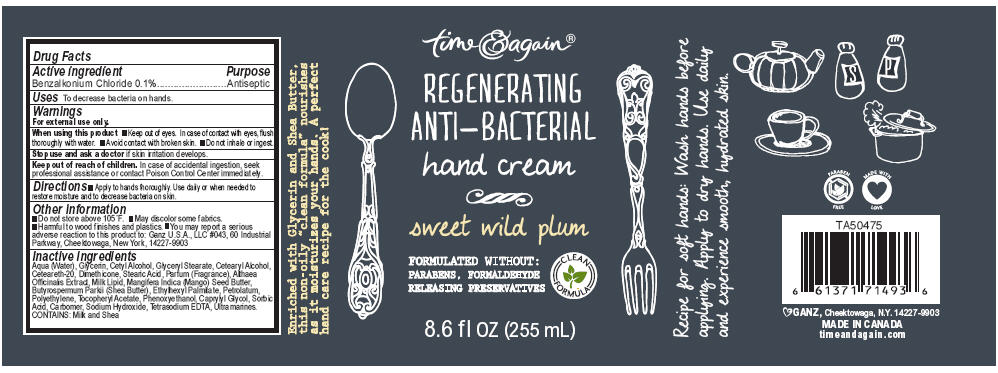 DRUG LABEL: Gourmet Kitchen Regenerating Anti-Bacterial 
NDC: 75862-019 | Form: LOTION
Manufacturer: GANZ U.S.A., LLC
Category: otc | Type: HUMAN OTC DRUG LABEL
Date: 20111207

ACTIVE INGREDIENTS: Benzalkonium Chloride 0.1 g/100 mL
INACTIVE INGREDIENTS: Water; Glycerin; Cetyl Alcohol; Glyceryl Monostearate; Cetostearyl Alcohol; Polyoxyl 20 Cetostearyl Ether; Dimethicone; Stearic Acid; Althaea Officinalis Root; Cow Milk Fat; Mangifera Indica Seed Butter; Shea Butter; Ethylhexyl Palmitate; Petrolatum; High Density Polyethylene; Alpha-Tocopherol Acetate; Phenoxyethanol; Caprylyl Glycol; Sorbic Acid; Carbomer Homopolymer Type C; Sodium Hydroxide; Edetate Sodium; Ultramarine Blue

time & again®
REGENERATING
ANTI-BACTERIAL
hand cream

Drug Facts

Active ingredient

Benzalkonium Chloride 0.1%

Purpose

Antiseptic

Uses

To decrease bacteria on hands.

Warnings

For external use only.

When using this product

- Keep out of eyes. In case of contact with eyes, flush thoroughly with water.
- Avoid contact with broken skin.
- Do not inhale or ingest.

Stop use and ask a doctor if skin irritation develops.

Keep out of reach of children. In case of accidental ingestion, seek professional assistance or contact Poison Control Center immediately.

Directions

- Apply to hands thoroughly. Use daily or when needed to restore moisture and to decrease bacteria on skin.

Other information

- Do not store above 105°F.
- May discolor some fabrics.
- Harmful to wood finishes and plastics.
- You may report a serious adverse reaction to this product to: Ganz U.S.A., LLC #043, 60 Industrial Parkway, Cheektowaga, New York, 14227-9903

Inactive ingredients

Aqua (Water), Glycerin, Cetyl Alcohol, Glyceryl Stearate, Cetearyl Alcohol, Ceteareth-20, Dimethicone, Stearic Acid, Parfum (Fragrance), Althaea Officinalis Extract, Milk Lipid, Mangifera Indica (Mango) Seed Butter, Butyrospermum Parkii (Shea Butter), Ethylhexyl Palmitate, Petrolatum, Polyethylene, Tocopheryl Acetate, Phenoxyethanol, Caprylyl Glycol, Sorbic Acid, Carbomer, Sodium Hydroxide, Tetrasodium EDTA, Ultramarines. CONTAINS: Milk and Shea

PRINCIPAL DISPLAY PANEL - 255 mL Bottle Label

time & again®

REGENERATING
ANTI-BACTERIAL
hand cream

fresh picked fig

FORMULATED WITHOUT:
PARABENS, FORMALDEHYDE
RELEASING PRESERVATIVES

CLEAN
FORMULA

8.6 fl oz (255 mL)

PRINCIPAL DISPLAY PANEL - 255 mL Bottle Label

time & again®

REGENERATING
ANTI-BACTERIAL
hand cream

sweet wild plum

FORMULATED WITHOUT:
PARABENS, FORMALDEHYDE
RELEASING PRESERVATIVES

CLEAN
FORMULA

8.6 fl oz (255 mL)